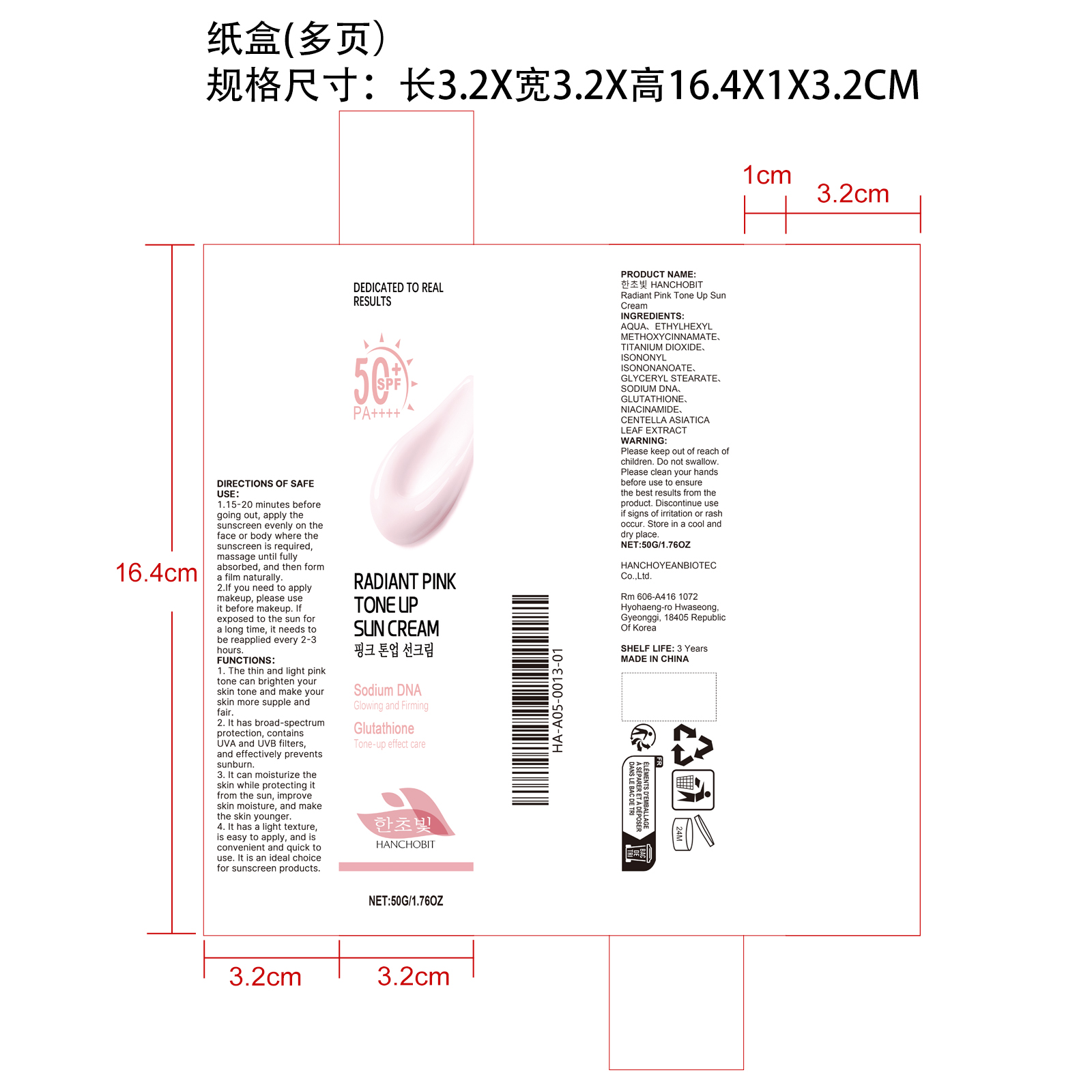 DRUG LABEL: HANCHOBIT Radiant Pink Tone Up Sun Cream
NDC: 85164-006 | Form: CREAM
Manufacturer: HANCHOYEANBIOTEC Co.,Ltd.
Category: otc | Type: HUMAN OTC DRUG LABEL
Date: 20251207

ACTIVE INGREDIENTS: CENTELLA ASIATICA LEAF 0.005 mg/50 mg
INACTIVE INGREDIENTS: GLYCERYL STEARATE 1 mg/50 mg; SODIUM PCA 0.05 mg/50 mg; NIACINAMIDE 0.05 mg/50 mg; TITANIUM DIOXIDE 2.5 mg/50 mg; ISONONYL ISONONANOATE 2 mg/50 mg; AQUA 39.845 mg/50 mg; GLUTATHIONE 0.05 mg/50 mg; ETHYLHEXYL METHOXYCINNAMATE 4.5 mg/50 mg

ACTIVE INGREDIENT

CENTELLA ASIATICA LEAF EXTRACT

PURPOSE

1. The thin and light pink tone can brighten your skin tone and make your skin more supple and fair.

2. It has broad-spectrum protection, contains UVA and UVB filters, and effectively prevents sunburn.

3. It can moisturize the skin while protecting it from the sun, improve skin moisture, and make the skin younger.

4. It has a light texture, is easy to apply, and is convenient and quick to use. It is an ideal choice for sunscreen products.

WHEN USING

1.15-20 minutes before going out, apply the sunscreen evenly on the face or body where the sunscreen is required, massage until fully absorbed, and then form a film naturally.
2.If you need to apply makeup, please use it before makeup. If exposed to the sun for a long time, it needs to be reapplied every 2-3 hours.

WARNINGS

Please keep out of reach of children. Do not swallow.Please clean your hands before use to ensure the best results from the product. Discontinue use if signs of irritation or rash occur. Store in a cool and dry place.

DO NOT USE

Discontinue use if signs of irritation or rash occur.

STOP USE

Discontinue use if signs of irritation or rash occur.

KEEP OUT OF REACH OF CHILDREN

Please keep out of reach of children. Do not swallow.

STORAGE AND HANDLING

Please keep out of reach of children. Do not swallow.

INACTIVE INGREDIENT

AQUA、ETHYLHEXYL METHOXYCINNAMATE、TITANIUM DIOXIDE、ISONONYL ISONONANOATE、GLYCERYL STEARATE、SODIUM DNA、GLUTATHIONE、NIACINAMIDE

DOSAGE AND ADMINISTRATION

1.15-20 minutes before going out, apply the sunscreen evenly on the face or body where the sunscreen is required, massage until fully absorbed, and then form a film naturally.
2.If you need to apply makeup, please use it before makeup. If exposed to the sun for a long time, it needs to be reapplied every 2-3 hours.

INDICATIONS AND USAGE

1.15-20 minutes before going out, apply the sunscreen evenly on the face or body where the sunscreen is required, massage until fully absorbed, and then form a film naturally.
2.If you need to apply makeup, please use it before makeup. If exposed to the sun for a long time, it needs to be reapplied every 2-3 hours.